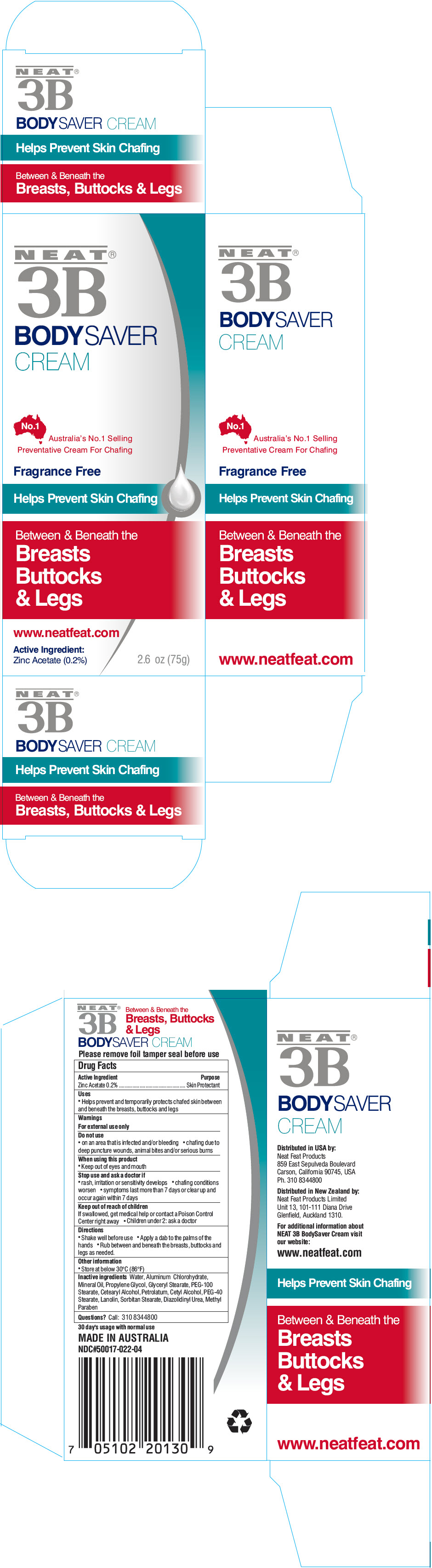 DRUG LABEL: Neat 3B Bodysaver
NDC: 50017-022 | Form: CREAM
Manufacturer: Neat Feat Products Limited
Category: otc | Type: HUMAN OTC DRUG LABEL
Date: 20231101

ACTIVE INGREDIENTS: ZINC ACETATE 0.15 g/75 g
INACTIVE INGREDIENTS: ALUMINUM CHLOROHYDRATE; PROPYLPARABEN; MINERAL OIL; WATER; PROPYLENE GLYCOL; GLYCERYL MONOSTEARATE; METHYLPARABEN; PEG-100 STEARATE; CETOSTEARYL ALCOHOL; PETROLATUM; CETYL ALCOHOL; PEG-40 STEARATE; LANOLIN; SORBITAN MONOSTEARATE; DIAZOLIDINYL UREA

NEAT® 3B BODYSAVER CREAM

Drug Facts

Active Ingredient

Zinc Acetate 0.2%

Purpose

Skin Protectant

Uses

- Helps prevent and temporarily protects chafed skin between and beneath the breasts, buttocks and legs

Warnings

For external use only

Do not use

- on an area that is infected and/or bleeding
- chafing due to deep puncture wounds, animal bites and/or serious burns

When using this product

- Keep out of eyes and mouth

Stop use and ask a doctor if

- rash, irritation or sensitivity develops
- chafing conditions worsen
- symptoms last more than 7 days or clear up and occur again within 7 days

Keep out of reach of children

If swallowed, get medical help or contact a Poison Control Center right away

- Children under 2: ask a doctor

Directions

- Shake well before use
- Apply a dab to the palms of the hands
- Rub between and beneath the breasts, buttocks and legs as needed.

Other information

- Store at below 30°C (86°F)

Inactive ingredients

Water, Aluminum Chlorohydrate, Mineral Oil, Propylene Glycol, Glyceryl Stearate, PEG-100 Stearate, Cetearyl Alcohol, Petrolatum, Cetyl Alcohol, PEG-40 Stearate, Lanolin, Sorbitan Stearate, Diazolidinyl Urea, Methylparaben, Propylparaben

Questions?

Call: 310 8344800

Distributed in USA by:
Neat Feat Products
859 East Sepulveda Boulevard
Carson, California 90745, USA

Distributed in New Zealand by:
Neat Feat Products Limited
Unit 13, 101-111 Diana Drive
Glenfield, Auckland 1310.

PRINCIPAL DISPLAY PANEL - 75 g Tube Box

NEAT®
3B

BODY SAVER
CREAM

No.1

Australia's No.1 Selling
Preventative Cream For Chafing

Fragrance Free

Helps Prevent Skin Chafing

Between & Beneath the
Breasts
Buttocks
& Legs

www.neatfeat.com

Active Ingredient:
Zinc Acetate (0.2%)
2.6 oz (75g)